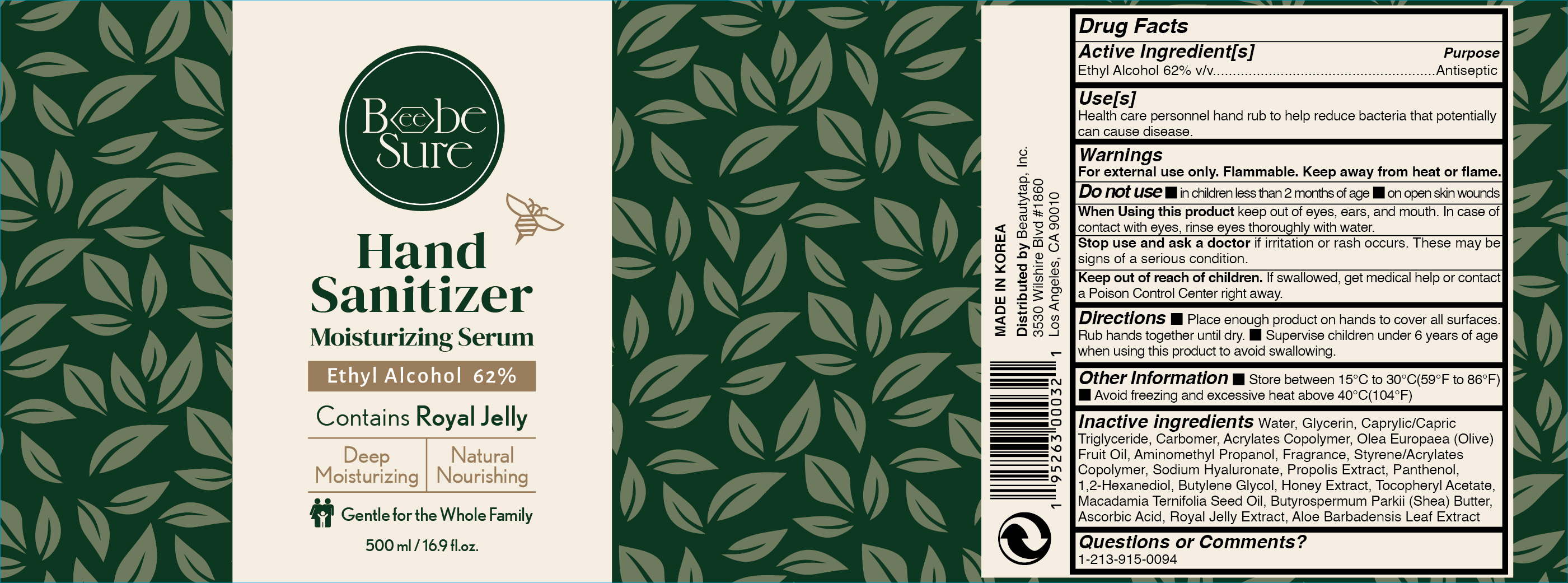 DRUG LABEL: BeebeSure Hand Sanitizer Moisturizing Serum 62% 500ml
NDC: 73862-220 | Form: LOTION
Manufacturer: E.CIS COSMETIC.Co.,Ltd
Category: otc | Type: HUMAN OTC DRUG LABEL
Date: 20201117

ACTIVE INGREDIENTS: ALCOHOL 62 mL/100 mL
INACTIVE INGREDIENTS: GLYCERIN; WATER; MEDIUM-CHAIN TRIGLYCERIDES; AMINOMETHYLPROPANOL; STYRENE/ACRYLAMIDE COPOLYMER (500000 MW); HYALURONATE SODIUM; 1,2-HEXANEDIOL; HONEY; MACADAMIA OIL; .ALPHA.-TOCOPHEROL ACETATE; BUTYL ACRYLATE/METHYL METHACRYLATE/METHACRYLIC ACID COPOLYMER (18000 MW); OLIVE OIL; CARBOMER 940; PROPOLIS WAX; PANTHENOL; BUTYLENE GLYCOL; ASCORBIC ACID; SHEA BUTTER; ROYAL JELLY; ALOE VERA LEAF

BeebeSure Hand Sanitizer Moisturizing Serum 62% 500ml

Active Ingredient(s)

Ethyl Alcohol 62% v/v. Purpose: Antiseptic

Purpose

Antiseptic, Hand Sanitizer

Use

Health care personnel hand rub to help reduce bacteria that potentially can cause disease.

Warnings

For external use only. Flammable. Keep away from heat or flame

Do not use

- in children less than 2 months of age
- on open skin wounds

When using this product keep out of eyes, ears, and mouth. In case of contact with eyes, rinse eyes thoroughly with water.

Stop use and ask a doctor if irritation or rash occurs. These may be signs of a serious condition.

Keep out of reach of children. If swallowed, get medical help or contact a Poison Control Center right away.

Directions

- Place enough product on hands to cover all surfaces. Rub hands together until dry.
- Supervise children under 6 years of age when using this product to avoid swallowing.

Other information

- Store between 15-30C (59-86F)
- Avoid freezing and excessive heat above 40C (104F)

Inactive ingredients

Water, Glycerin, Caprylic/Capric Triglyceride, Carbomer, Acrylates Copolymer, Olea Europaea (Olive) Fruit Oil, Aminomethyl Propanol, Fragrance, Styrene/Acrylates Copolymer, Sodium Hyaluronate, Propolis Extract, Panthenol, 1,2-Hexanediol, Butylene Glycol, Tocopheryl Acetate, Macadamia Ternifolia Seed Oil, Honey Extract, Butyrospermum Parkii (Shea) Butter, Ascorbic Acid, Royal Jelly Extract, Aloe Barbadensis Leaf Extract

Package Label - Principal Display Panel

BeebeSure
Hand Sanitizer Moisturizing Serum
Ethyl Alcohol 62%
Contains Royal Jelly
Deep Moisturizing Natural Nourishing
Gentle for the Whole Family
500 mL / 16.9 fl. oz.